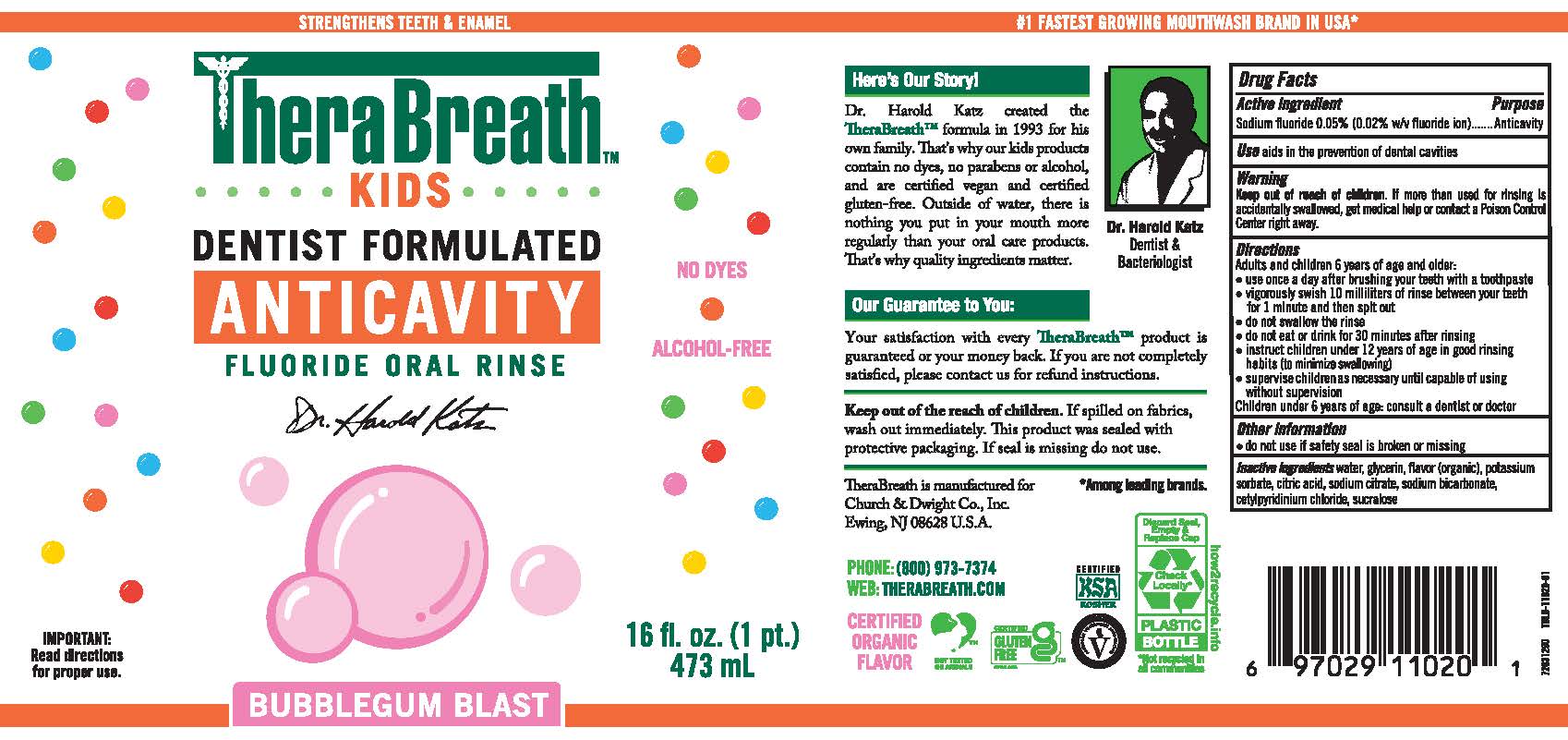 DRUG LABEL: TheraBreath Kids Anticavity Oral Rinse Bubblegum
NDC: 10237-266 | Form: RINSE
Manufacturer: Church & Dwight Co., Inc.
Category: otc | Type: HUMAN OTC DRUG LABEL
Date: 20241121

ACTIVE INGREDIENTS: SODIUM FLUORIDE 0.005 mg/10 mL
INACTIVE INGREDIENTS: WATER; CITRIC ACID MONOHYDRATE; SUCRALOSE; SODIUM BICARBONATE; CETYLPYRIDINIUM CHLORIDE; GLYCERIN; POTASSIUM SORBATE

TheraBreath Kids Anticavity Bubblegum

ACTIVE INGREDIENT

Sodium fluoride 0.05% (0.02% w/v fluoride ion)

PURPOSE

Anticavity

USE

aids in the prevention of dental cavities

Warning

Keep out of reach of children. If more than used for rinsing is accidentally swallowed, get medical help or contact a Poison Control Center right away.

DIRECTIONS

Adults and children 6 years of age and older:
• use once a day after brushing your teeth with a toothpaste
• vigorously swish 10 milliliters of rinse between your teeth
for 1 minute and then spitout
•do not swallow the rinse
• do not eat or drink for30 minutes after rinsing
• instruct children under 12 years of age in good rinsing
habits (to minimize swallowing)
• supervise childrenas necessary until capableof using
without supervision
Children under 6 years of age: consult a dentist or doctor

OTHER INFORMATION

- do not use if safety seal is broken or missing

INACTIVE INGREDIENTS

water, glycerin, flavor (organic), potassium sorbate,citric acid, sodium citrate, sodium bicarbonate, cetylpyridinium chloride, sucralose

PACKAGE LABEL

STRENGTHENS TEETH & ENAMEL

TheraBreath

KIDS

DENTIST FORMULATED

ANTICAVITY

FLUORIDE ORAL RINSE

Dr. Harold Katz

Bubblegum Blast

No DYES

ALCOHOL-FREE

IMPORTANT: Read direcations for proper use.

16 fl. oz. (1 pt.) 473 mL